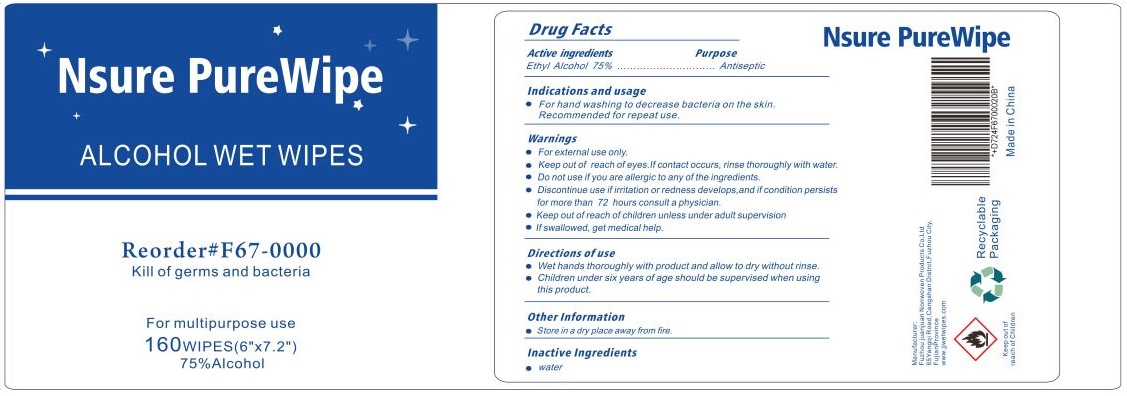 DRUG LABEL: Nsure PureWipe ALCOHOL WET WIPES
NDC: 54141-003 | Form: CLOTH
Manufacturer: Fuzhou Juanjuan Non-Woven Products Co., Ltd.
Category: otc | Type: HUMAN OTC DRUG LABEL
Date: 20210208

ACTIVE INGREDIENTS: ALCOHOL 75 mL/100 mL
INACTIVE INGREDIENTS: WATER

Nsure PureWipe ALCOHOL WET WIPES

Active ingredients

Ethyl Alcohol 75%

Purpose

Antiseptic

Indications and usage

• For hand washing to decrease bacteria on the skin.
Recommended for repeat use.

Warnings

- For external use only.
- Keep out of reach of eyes. If contact occurs, rinse thoroughly with water.
- Do not use if you are allergic to any of the ingredients.
- Discontinue use if irritation or redness develops, and if condition persists for more than 72 hours consult a physician.

- Keep out of reach of children unless under adult supervision
- If swallowed, get medical help.

Directions of use

- Wet hands thoroughly with product and allow to dry without rinse.
- Children under six years of age should be supervised when using this product.

Other Information

- Store in a dry place away from fire.

Inactive Ingredients

- water

Kill of germs and bacteria

For multipurpose use

75%Alcohol

Manufacturer:

Fuzhou juanjuan Nonwoven Products Co, Ltd

65Yangqi Road, Cangshan District, Fuzhou City,

FujianProvince

www.jjwetwipes.com

Keep out of reach of Children

Made in China